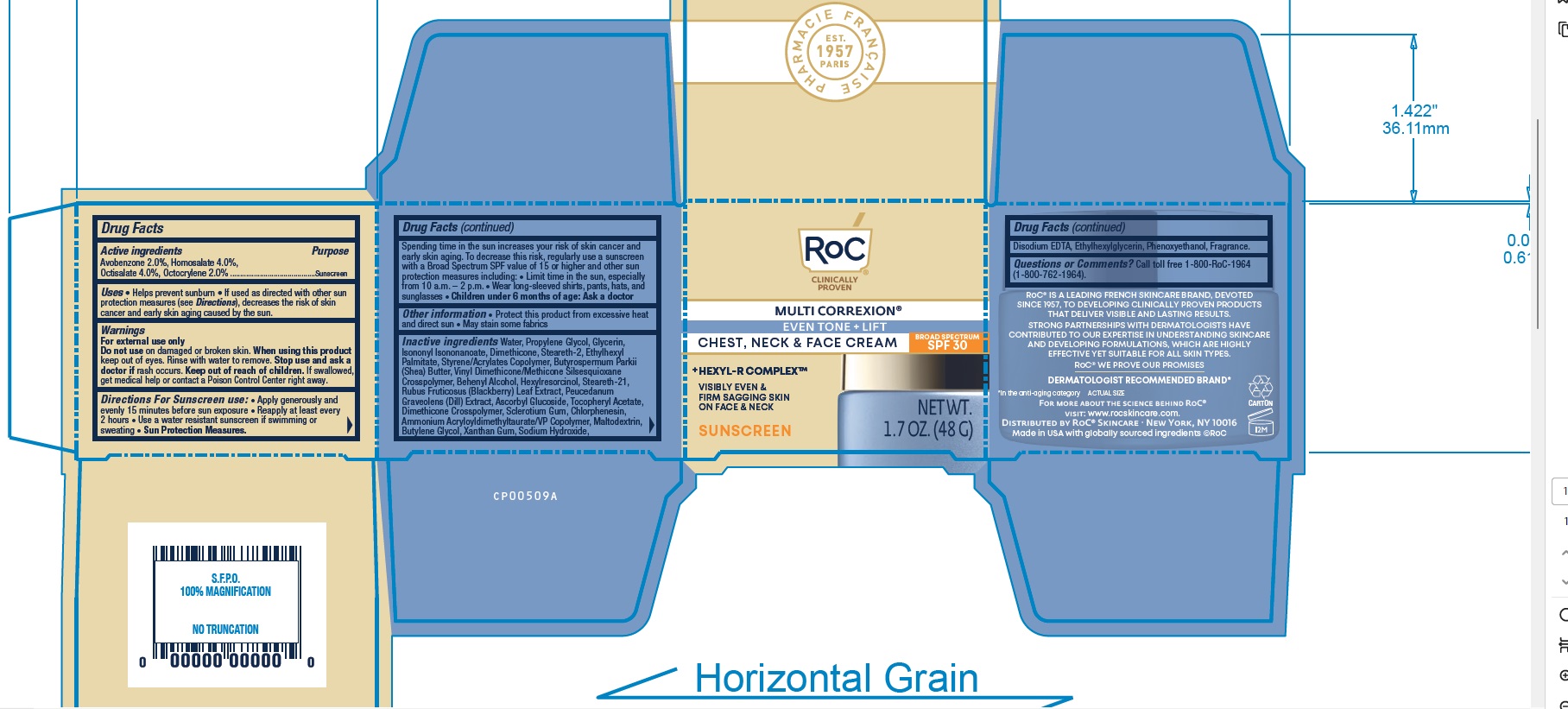 DRUG LABEL: ROC MULTI CORREXION - EVEN TONE AND LIFT - 5-In-1 Chest, Neck, and Face Cream Sunscreen - Broad Spectrum SPF 30
NDC: 73496-008 | Form: LOTION
Manufacturer: Roc Skincare
Category: otc | Type: HUMAN OTC DRUG LABEL
Date: 20251201

ACTIVE INGREDIENTS: HOMOSALATE 4 mg/100 g; OCTISALATE 4 mg/100 g; OCTOCRYLENE 2 mg/100 g; AVOBENZONE 2 mg/100 g
INACTIVE INGREDIENTS: DIMETHICONE CROSSPOLYMER; VINYL DIMETHICONE/METHICONE SILSESQUIOXANE CROSSPOLYMER; MALTODEXTRIN; DOCOSANOL; ETHYLHEXYLGLYCERIN; PROPYLENE GLYCOL; GLYCERIN; DIMETHICONE; SODIUM HYDROXIDE; HEXYLRESORCINOL; WATER; STEARETH-2; STEARETH-21; ISONONYL ISONONANOATE; BETASIZOFIRAN; AMMONIUM ACRYLOYLDIMETHYLTAURATE/VP COPOLYMER; ASCORBYL GLUCOSIDE; SHEA BUTTER; ETHYLHEXYL PALMITATE; EDETATE DISODIUM; .ALPHA.-TOCOPHEROL ACETATE; PHENOXYETHANOL; DILL; BUTYLENE GLYCOL; XANTHAN GUM; STYRENE/ACRYLAMIDE COPOLYMER (MW 500000); RUBUS FRUTICOSUS LEAF; CHLORPHENESIN

ROC MULTI CORREXION - EVEN TONE + LIFT- 5-In-1 Chest, Neck, & Face Cream Sunscreen - Broad Spectrum SPF 30

ACTIVE INGREDIENT

Avobenzone 2.0%, Homosalate 4.0%, Octisalate 4.0%, Octocrylene 2.0%

PURPOSE

Sunscreen

Uses

- Helps prevent sunburn
- If used as directed with other sun protection measures (see Directions), decreases the risk of skin cancer and early skin aging caused by the sun

Warnings

For external use only
Do not use on damaged or broken skin. When using this product keep out of eyes. Rinse with water to remove. Stop use and ask a doctor if rash occurs. Keep out of reach of children. If swallowed, get medical help or contact Poison Control Center right away

Keep out of reach of children.

Directions

- Apply generously and evenly 15 minutes before sun exposure
- Reapply at least every 2 hours
- Use a water resistant sunscreen if swimming or sweating
- Sun Protection Measures. Spending time in the sun increases your risk of skin cancer and early skin aging. To decrease this risk, regularly use a sunscreen with a Broad Spectrum SPF 15 or higher and other sun protection measures including:
- Limit time in the sun, especially from 10 a.m. - 2 p.m.
- Wear long-sleeved shirts, pants, hats, and sunglasses
- Children under 6 months of age: Ask a doctor

Other information

- Protect this product from excessive heat and direct sun
- May stain some fabrics

INACTIVE INGREDIENT

Water, Propylene Glycol, Glycerin, Isononyl Isononanoate, Dimethicone, Steareth-2, Ethylhexyl Palmitate, Styrene/Acrylates Copolymer, Butyrospermum Parkii (Shea) Butter, Vinyl Dimethicone/Methicone Silsesquioxane Crosspolymer, Behenyl Alcohol, Hexylresorcinol, Steareth-21, Rubus Fruticosus (Blackberry) Leaf Extract, Peucedanum Graveolens (Dill) Extract, Ascorbyl Glucoside, Tocopheryl Acetate, Dimethicone Crosspolymer, Sclerotium Gum, Chlorphenesin, Ammonium Acryloyldimethyltaurate/VP Copolymer, Maltodextrin, Butylene Glycol, Xanthan Gum, Sodium Hydroxide, Disodium EDTA, Ethylhexylglycerin, Phenoxyethanol, Fragrance.

Questions or Comments?

Call toll free 1-800-RoC-1964 (1-800-762-1964) or 215-273-8755 (collect).